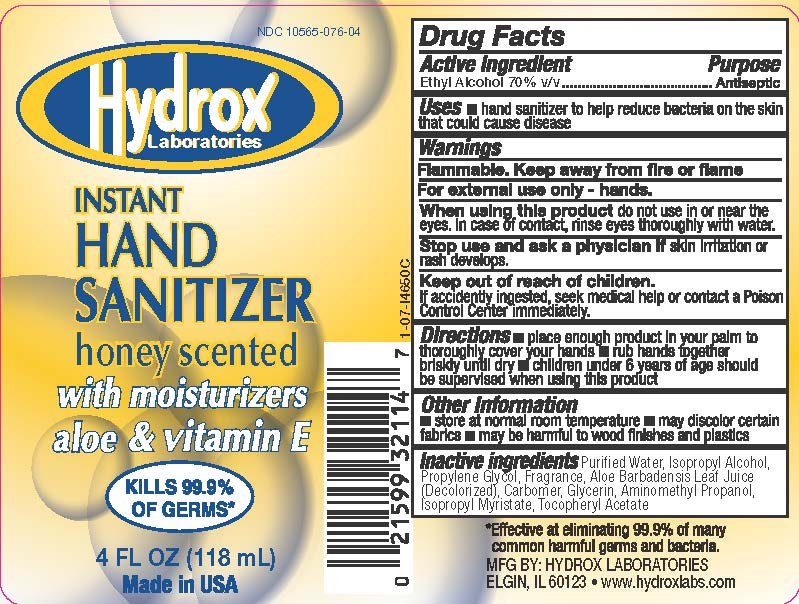 DRUG LABEL: Instant Hand Sanitizer
NDC: 10565-076 | Form: GEL
Manufacturer: Hydrox Laboratories
Category: otc | Type: HUMAN OTC DRUG LABEL
Date: 20260112

ACTIVE INGREDIENTS: ALCOHOL 70 mL/100 mL
INACTIVE INGREDIENTS: CARBOMER HOMOPOLYMER TYPE C; GLYCERIN; ISOPROPYL ALCOHOL; ISOPROPYL MYRISTATE; PROPYLENE GLYCOL; WATER; ALPHA-TOCOPHEROL ACETATE; ALOE VERA LEAF; AMINOMETHYLPROPANOL

Instant Hand Sanitizer

Drug Facts

Active ingredient

Ethyl Alcohol 70% v/v

Purpose

Antiseptic

Uses

- hand sanitizer to help reduce bacteria on the skin that could cause disease

Warnings

Flammable. Keep away from fire or flame

WHEN USING

For external use only - hands.

When using this productdo not use in or near the eyes. In case of contact, rinse eyes thoroughly with water.

Stop use and ask a physician ifskin irritation or rash develops.

Keep out of reach of children.If accidently ingested, seek medical help or contact a Poison Control Center immediately.

Directions

- place enough product in your palm to thoroughly cover your hands
- rub hands together briskly until dry
- children under 6 years of age should be supervised when using this product

Other Information

- store at normal room temperature
- may discolor certain fabrics
- may be harmful to wood finishes and plastics

Inactive ingredients

carbomer, fragrance, glycerin, isopropyl alcohol, isopropyl myristate, propylene glycol, purified water, tocopheryl acetate, aloe vera gel, AMP-95

MFG BY: HYDROX LABORATORIES
825 Tollgate Road ELGIN, IL 60123

PRINCIPAL DISPLAY PANEL

NDC 10565-076-04

Hydrox
Laboratories

INSTANT
HAND
SANITIZER
with moisturizers
aloe & vitamin E

KILLS 99.9%
OF GERMS*

4 FL OZ 118 mL

Made in USA